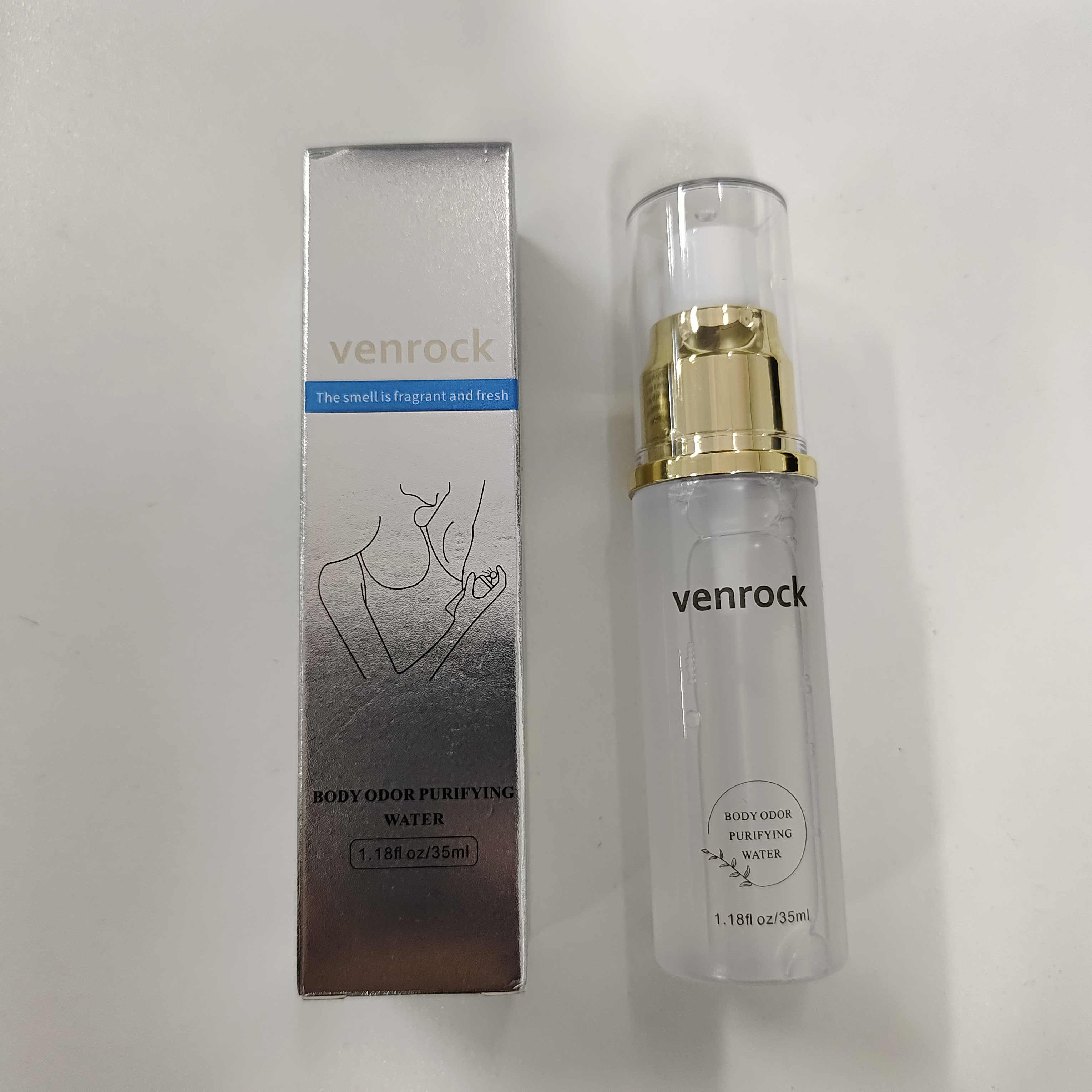 DRUG LABEL: VENROCK
NDC: 85772-0003 | Form: SPRAY
Manufacturer: Guangzhou Oupeng Cosmetics Co., Ltd.
Category: otc | Type: HUMAN OTC DRUG LABEL
Date: 20250625

ACTIVE INGREDIENTS: ALUMINUM CHLOROHYDRATE 10 g/100 g
INACTIVE INGREDIENTS: LEONTOPODIUM ALPINUM 0.2 g/100 g; PIPER METHYSTICUM ROOT 0.095 g/100 g; STEPHANIA TETRANDRA ROOT 0.09 g/100 g; 1,3-BUTYLENE GLYCOL 1-PROPIONATE 5 g/100 g; GENTIANA SCABRA ROOT 0.05 g/100 g; ETHYLHEXYLGLYCERIN 0.3 g/100 g; DIPROPYLENE GLYCOL 3 g/100 g; METHYLPARABEN 0.15 g/100 g; CALCIUM DISODIUM EDTA 0.1 g/100 g; PEG-40 HYDROGENATED CASTOR OIL 1.5 g/100 g; FRAGRANCE 13576 0.04 g/100 g; AQUA 79.395 g/100 g; CAPRYLHYDROXAMIC ACID 0.08 g/100 g

Active ingredient

Aluminum Chlorohydrate 10%

Purpose

Antiperspirant

Uses

Reduces underarm wetness

Warnings

For external use only.

Do not use

On broken skin

Ask a doctor before use if you have

Kidney disease

When using this product

Do not get into eyes. If contact occurs, rinse eyes thoroughly with water.

Stop use and ask a doctor if

Rash or irritation develops and persists.

Pregnancy or breast feeding section

If pregnant or breast-feeding, ask a health professional before use.

Keep out of reach of children

In case of accidental ingestion, get medical help or contact a Poison Control Center right away.

Directions

- For external use on armpits only.
- Take an appropriate amount of this product and spray evenly on the armpits.
- Use daily after bathing for best results.

Other information

Store in a cool, dry place. Avoid direct sunlight and high temperatures. Seal the container tightly after use.

Inactive ingredients

AQUA, BUTYLENE GLYCOL, PROPYLENE GLYCOL, PEG-40 HYDROGENATED CASTOR OIL, ETHYLHEXYLGLYCERIN, LEONTOPODIUM ALPINUM EXTRACT, METHYLPARABEN, DISODIUM EDTA, PIPER METHYSTICUM LEAF/ROOT/STEM EXTRACT, STEPHANIA TETRANDRA ROOT EXTRACT, CAPRYLHYDROXAMIC ACID, GENTIANA SCABRA EXTRACT, PARFUM

Questions or comments?

934-935-7135 / Yiqinzhi726@gmail.com

Box Front Panel

VENROCK
BODY ODOR PURIFYING WATER
The smell is fragrant and fresh Antiperspirant
1.18 fl.oz / 35 ml